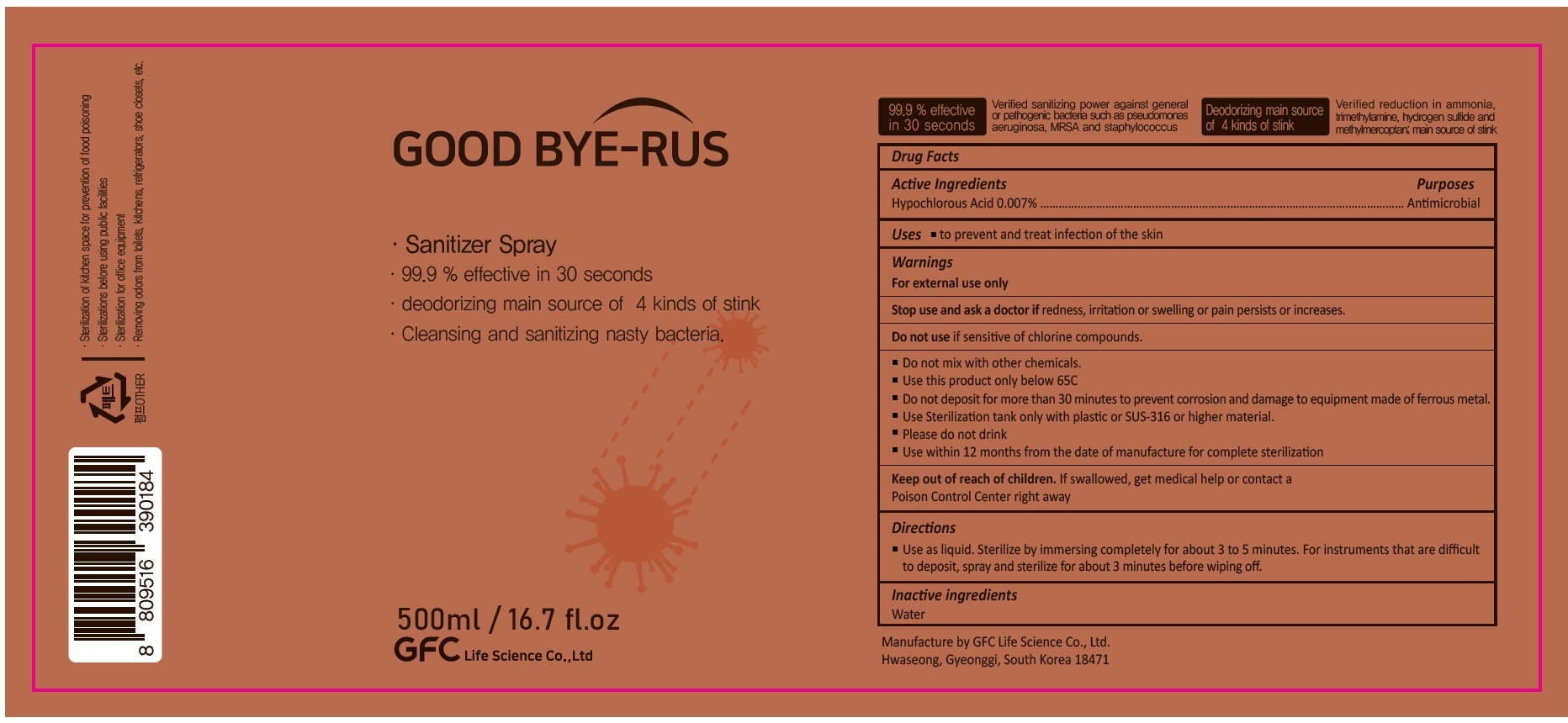 DRUG LABEL: GOOD BYE-RUS
NDC: 76836-003 | Form: SPRAY
Manufacturer: GFC Life Science Co., Ltd.
Category: otc | Type: HUMAN OTC DRUG LABEL
Date: 20200720

ACTIVE INGREDIENTS: HYPOCHLOROUS ACID 0.00007 g/1 mL
INACTIVE INGREDIENTS: WATER

76836-003_GOOD BYE-RUS

Active ingredient

HYPOCHLOROUS ACID 0.007%

Purpose

Antimicrobial

Use

- Prevent and treat infection of the skin

Warnings

For external use only

Do not use if sensitive of chlorine compounds.

Stop use and ask a doctor if redness, irritation or swelling or pain persists or increases.

Keep out of reach of children. If swallowed, get medical help or contact a Poison Control Center right away.

Directions

- Use as liquid. Sterilize by immersing completely for about 3 to 5 minutes. For instruments that are difficult to deposit, spray and sterilize for about 3 minutes before wiping off.

Inactive ingredients

Water